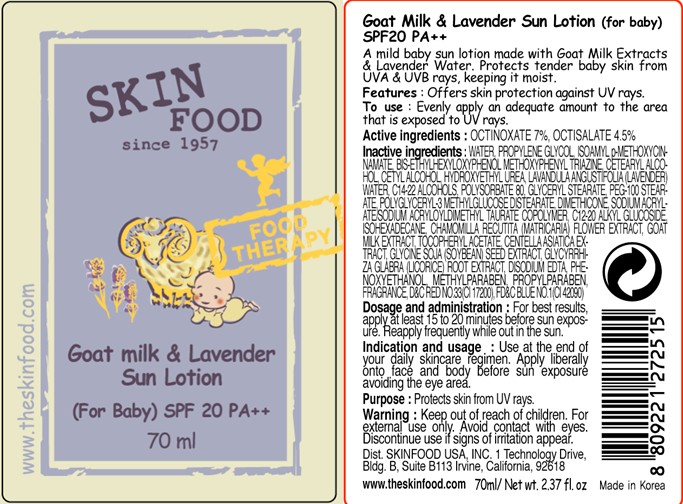 DRUG LABEL: GOAT MILK AND LAVENDER SUN
NDC: 76214-033 | Form: LOTION
Manufacturer: SKINFOOD CO., LTD.
Category: otc | Type: HUMAN OTC DRUG LABEL
Date: 20111004

ACTIVE INGREDIENTS: OCTINOXATE 4.9 mL/70 mL; OCTISALATE 3.15 mL/70 mL
INACTIVE INGREDIENTS: WATER; PROPYLENE GLYCOL; CETOSTEARYL ALCOHOL; CETYL ALCOHOL; HYDROXYETHYL UREA; LAVANDULA ANGUSTIFOLIA FLOWERING TOP; C14-22 ALCOHOLS; POLYSORBATE 80; GLYCERYL MONOSTEARATE; PEG-100 STEARATE; DIMETHICONE; PHENOXYETHANOL; C12-20 ALKYL GLUCOSIDE; METHYLPARABEN; ISOHEXADECANE; CHAMOMILE; GOAT MILK; PROPYLPARABEN; CENTELLA ASIATICA; SOYBEAN; GLYCYRRHIZA GLABRA; EDETATE DISODIUM

Drug Facts

Active ingredients: OCTINOXATE 7%, OCTISALATE 4.5%

Inactive ingredients:
WATER, PROPYLENE GLYCOL, ISOAMYL p-METHOXYCINNAMATE, BIS-ETHYLHEXYLOXYPHENOL METHOXYPHENYL TRIAZINE, CETEARYL ALCOHOL, CETYL ALCOHOL, HYDROXYETHYL UREA, LAVANDULA ANGUSTIFOLIA (LAVENDER) WATER, C14-22 ALCOHOLS, POLYSORBATE 80, GLYCERYL STEARATE, PEG-100 STEARATE, POLYGLYCERYL-3 METHYLGLUCOSE DISTEARATE, DIMETHICONE, SODIUM ACRYLATE/SODIUM ACRYLOYLDIMETHYL TAURATE COPOLYMER, C12-20 ALKYL GLUCOSIDE, ISOHEXADECANE, CHAMOMILLA RECUTITA (MATRICARIA) FLOWER EXTRACT, GOAT MILK EXTRACT, TOCOPHERYL ACETATE, CENTELLA ASIATICA EXTRACT, GLYCINE SOJA (SOYBEAN) SEED EXTRACT, GLYCYRRHIZA GLABRA (LICORICE) ROOT EXTRACT, DISODIUM EDTA, PHENOXYETHANOL, METHYLPARABEN, PROPYLPARABEN, FRAGRANCE

Purpose: Protects skin from UV rays.

Warnings:
For external use only.
Avoid contact with eyes.
Discontinue use if signs of irritation appear.

Keep out of reach of children:
Keep out of reach of children.

Indication and usage:
Use at the end of your daily skincare regimen.
Apply liberally onto face and body before sun exposure avoiding the eye area.

Dosage and administration:
For best results, apply at least 15 to 20 minutes before sun exposure.
Reapply frequently while out in the sun.